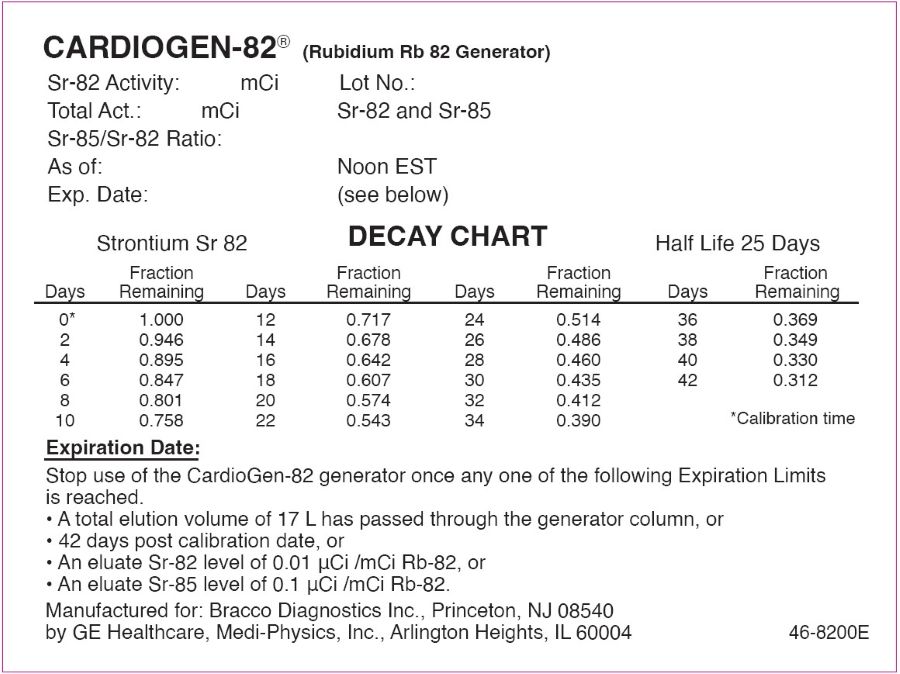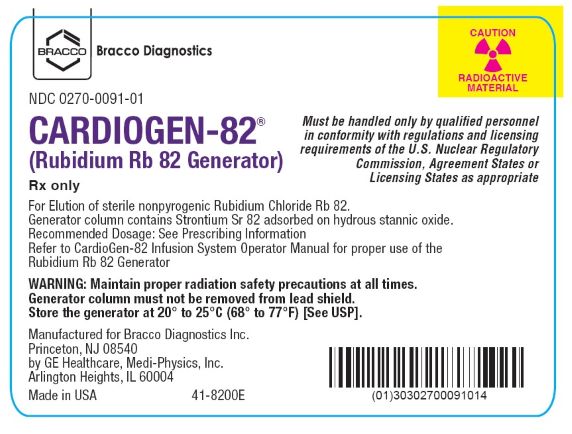 DRUG LABEL: CardioGen-82
NDC: 0270-0091 | Form: INJECTION, SOLUTION
Manufacturer: Bracco Diagnostics Inc
Category: prescription | Type: HUMAN PRESCRIPTION DRUG LABEL
Date: 20250813

ACTIVE INGREDIENTS: RUBIDIUM CHLORIDE RB-82 150 mCi/1 1

HIGHLIGHTS OF PRESCRIBING INFORMATION

These highlights do not include all the information needed to use CARDIOGEN-82 safely and effectively. See full prescribing information for CARDIOGEN-82.
CARDIOGEN-82® (rubidium Rb 82 generator) to produce rubidium chloride Rb 82 injection, for intravenous use
Initial U.S. Approval: 1989

WARNING: HIGH LEVEL RADIATION EXPOSURE WITH USE OF INCORRECT ELUENT and FAILURE TO FOLLOW THE ELUATE TESTING PROTOCOL

See full prescribing information for complete boxed warning.

High Level Radiation Exposure with Use of Incorrect Eluent
Using the incorrect eluent can cause high Strontium (Sr) 82 and Sr 85 breakthrough levels.

- Use only additive-free 0.9% Sodium Chloride Injection to elute CardioGen-82.
- If an incorrect solution is used to elute CardioGen-82:
  - Immediately stop the patient infusion;
  - Evaluate the patient’s radiation absorbed dose and monitor for the effects of radiation to critical organs such as bone marrow;
  - Permanently discontinue use of the affected generator. (2.5, 2.10, 5.1)

Excess Radiation Exposure with Failure to Follow the Eluate Testing Protocol
Excess radiation exposure occurs when the levels of Sr 82 or Sr 85 in the Rubidium Chloride Rb 82 Injection exceed limits.

- Record eluate volume, including waste and test volumes.
- Strictly adhere to the generator eluate testing protocol.
- Stop using the generator if it reaches any of its Expiration Limits. (2.5, 2.6, 2.7, 2.8, 5.2)

RECENT MAJOR CHANGES

Dosage and Administration,

12/2024

Dosing and Administration of Rubidium Chloride Rb 82 Injection (2.2)

Infusion System (2.4)

1 INDICATIONS AND USAGE

CardioGen-82, used to produce Rubidium Chloride Rb 82 Injection, is a radioactive diagnostic agent indicated for positron emission tomography (PET) of the myocardium under rest or pharmacologic stress conditions to evaluate regional myocardial perfusion in adult patients with suspected or existing coronary artery disease.

2 DOSAGE AND ADMINISTRATION

- Dosing when using the Model 510 Infusion System: 1,480 MBq (40 mCi), with a range of 1,110 MBq to 2,220 MBq (30 mCi to 60 mCi) per rest or stress component of a procedure via intravenous infusion at 50 mL/min. (2.2)
- Dosing when using the Model 1700 Infusion System: 10 MBq/kg to 30 MBq/kg actual body weight (0.27 mCi/kg to 0.81 mCi/kg) per rest or stress component of a procedure via intravenous infusion at 50 mL/minute or 20 mL/minute. (2.2)
- Do not exceed a maximum dose of 2,220 MBq (60 mCi) or a maximum volume of 100 mL per rest or stress component of a procedure. (2.2)
- The minimum interval between the rest and stress doses is 10 minutes to allow sufficient Rb 82 decay. (2.2)
- Start image acquisition 60 seconds to 90 seconds after completion of the infusion; if a longer circulation time is anticipated, wait for 120 seconds. Image acquisition is 5 minutes long. (2.3)
- For radiation safety, infusion systems, elution instruction, eluate testing, dose delivery, and expiration limits of CardioGen-82, and radiation dosimetry see full prescribing information. (2.1, 2.5, 2.6,2.7, 2.8, 2.9, 2.10)

3 DOSAGE FORMS AND STRENGTHS

Rubidium Rb 82 generator used to produce Rubidium Chloride Rb 82 Injection: 3,330 MBq to 5,550 MBq (90 mCi to 150 mCi) of strontium-82 (Sr 82) at calibration time, adsorbed on a hydrous stannic oxide column. (3)

4 CONTRAINDICATIONS

None. (4)

5 WARNINGS AND PRECAUTIONS

Risk Associated with Pharmacological Stress: Pharmacologic induction of cardiovascular stress may cause serious adverse reactions such as myocardial infarction, arrhythmia, hypotension, broncho-constriction, and cerebrovascular events. Perform testing only in setting where cardiac resuscitation equipment and trained staff are readily available. (5.3)

6 ADVERSE REACTIONS

To report SUSPECTED ADVERSE REACTIONS, contact Bracco Diagnostics Inc. at 1-800-257-8151 or FDA at 1-800-FDA-1088 or www.fda.gov/medwatch.

8 USE IN SPECIFIC POPULATIONS

Lactation: Do not resume breastfeeding until at least one hour after administration of Rubidium Chloride Rb 82 Injection. (8.2)

FULL PRESCRIBING INFORMATION

WARNING: HIGH LEVEL RADIATION EXPOSURE WITH USE OF INCORRECT ELUENT and FAILURE TO FOLLOW THE ELUATE TESTING PROTOCOL

High Level Radiation Exposure with Use of Incorrect Eluent
Patients are exposed to high radiation levels when the CardioGen-82 generator is eluted with the incorrect eluent due to high strontium (Sr) 82 and Sr 85 breakthrough levels.

- Use only additive-free 0.9% Sodium Chloride Injection to elute the generator.
- If an incorrect solution is used to elute the CardioGen-82 generator:
  - Immediately stop the patient infusion;
  - Evaluate the patient’s radiation absorbed dose, and monitor for the effects of radiation to critical organs such as bone marrow;
  - Permanently discontinue the use of the affected generator [see Dosage and Administration (2.5) and Warnings and Precautions (5.1)].

Excess Radiation Exposure with Failure to Follow the Eluate Testing Protocol
Excess radiation exposure occurs when the levels of Sr 82 or Sr 85 in the Rubidium Chloride Rb 82 Injection exceed specified limits.

- Record each generator eluate volume, including waste and test volumes, and keep a record of the cumulative eluate volume.
- Strictly adhere to the generator eluate testing protocol, to minimize the risk of excess radiation exposure, including daily testing and additional testing at Alert Limits.
- Stop using the generator if it reaches any of its Expiration Limits:
  - 17 L for the generator’s cumulative eluate volume
  - 42 days post generator calibration date
  - An eluate Sr 82 level of 0.01 microCi /mCi Rb 82
  - An eluate Sr 85 level of 0.1 microCi /mCi Rb 82 [see Dosage and Administration (2.5, 2.6, 2.7, 2.8) and Warnings and Precautions (5.2)]

1 INDICATIONS AND USAGE

CardioGen-82, used to produce Rubidium Chloride Rb 82 Injection, is indicated for positron emission tomography (PET) of the myocardium under rest or pharmacologic stress conditions to evaluate regional myocardial perfusion in adult patients with suspected or existing coronary artery disease.

2 DOSAGE AND ADMINISTRATION

2.1 Radiation Safety - Drug Handling

CardioGen-82, when eluted with additive-free 0.9% Sodium Chloride Injection, produces Rubidium Chloride Rb 82 Injection. Handle CardioGen-82, Rubidium Chloride Rb 82 Injection, and Infusion Systems with appropriate safety measures to minimize radiation exposure. Wear waterproof gloves and effective shielding throughout the entire preparation and handling [See Warnings and Precautions (5.4)].

Limit the use of radiopharmaceuticals to healthcare providers who are qualified by specific training and experience in the safe use and handling of radionuclides and whose experience and training have been approved by the appropriate government agency authorized to license the use of radionuclides.

2.2 Dosing and Administration of Rubidium Chloride Rb 82 Injection

Important Dosing and Administration Instructions

- Observe aseptic techniques in all drug handling and administration.
- Use CardioGen-82 with the CardioGen-82 Infusion System to elute and administer Rubidium Chloride Rb 82 Injection.
- There are two infusion systems that are different in dosing, elution, and eluate testing. Ensure use of the correct infusion system when following the instructions for dosing, elution, and eluate testing.
- Use the lowest dose necessary, consistent with the goal of as low as reasonably achievable (ALARA), to obtain adequate cardiac visualization based on patient body weight and the imaging equipment and acquisition methodology used to perform the procedure. For example, 3D image acquisition may require doses at the lower end of the recommended range, compared to 2D imaging.
- Administer two single doses to complete rest and stress myocardial perfusion imaging (MPI) [see Dosage and Administration (2.3)].
- The minimum interval between the rest and stress doses is 10 minutes to allow sufficient Rb 82 decay.
- Instruct patients to void as soon as a study is completed and as often as possible thereafter for at least one hour [see Warnings and Precautions (5.4)].

Dosing When Using the CardioGen-82 Model 510 Infusion System

The recommended dose of Rubidium Chloride Rb 82 Injection per rest or stress component of a PET MPI procedure in adults is 1,480 MBq (40 mCi), with a range of 1,110 MBq to 2,220 MBq (30 mCi to 60 mCi), administered by intravenous infusion at 50 mL/minute through a catheter inserted into a large peripheral vein.

Do not exceed a maximum dose of 2,220 MBq (60 mCi) or a maximum volume of 100 mL per rest or stress component of a procedure.

Dosing When Using the CardioGen-82 Model 1700 Infusion System

The recommended dose of Rubidium Chloride Rb 82 Injection per rest or stress component of a PET MPI procedure in adults is 10 MBq/kg to 30 MBq/kg actual body weight (0.27 mCi/kg to 0.81 mCi/kg) administered by intravenous infusion at 50 mL/minute or 20 mL/minute through a catheter inserted into a large peripheral vein.

Do not exceed a maximum dose of 2,220 MBq (60 mCi) or a maximum volume of 100 mL per rest or stress component of a procedure.

2.3 Image Acquisition Instructions

Rest Imaging

- Administer a single dose of Rubidium Chloride Rb 82 Injection.
- Start imaging 60 seconds to 90 seconds after completion of the first dose infusion and acquire images for 5 minutes.

Stress Imaging

- Begin the study at least 10 minutes after completion of the resting dose infusion, to allow for sufficient Rb 82 decay.
- Administer a pharmacologic stress agent in accordance with its prescribing information.
- After the administration of the pharmacologic stress agent, administer the second dose of Rubidium Chloride Rb 82 Injection at the time interval according to the prescribing information of the pharmacologic stress agent.
- Start imaging 60 seconds to 90 seconds after completion of the second dose infusion and acquire images for 5 minutes.

Rest and Stress Imaging

- If a longer circulation time is anticipated (e.g., in a patient with severe left ventricular dysfunction), start imaging 120 seconds after the dose.
- Acquisition may be started immediately post-injection if dynamic imaging is needed.

2.4 Infusion System

- Use CardioGen-82 only with the CardioGen-82 Infusion System Model 510 or the CardioGen-82 Infusion System Model 1700, which are specifically designed for use with the generator and capable of accurate measurement and delivery of doses of Rubidium Chloride Rb 82 Injection.
- Follow instructions in the CardioGen-82 Infusion System Model 510 or Model 1700 Operator’s Manual for the set up and administration of Rubidium Chloride Rb 82 Injection.
- The CardioGen-82 Infusion System Model 510 provides ± 10% accuracy for measuring Rubidium Chloride Rb 82 Injection doses of 1,110 MBq to 2,220 MBq (30 mCi to 60 mCi).
- The CardioGen-82 Infusion System Model 1700 provides ± 10% accuracy for measuring Rubidium Rb 82 Chloride Injection doses of 1,110 MBq to 2,220 MBq (30 mCi to 60 mCi), and ± 15% accuracy for doses of 370 MBq to 1,110 MBq (10 mCi to 30 mCi).

2.5 Directions for Eluting Rubidium Chloride Rb 82 Injection

- Use only additive-free 0.9 % Sodium Chloride Injection to elute the generator [see Warnings and Precautions (5.1)].
- Prepare the 0.9 % Sodium Chloride Injection for use with the Saline Tag
  - Prepare the intravenous port in accordance with the approved prescribing information of the 0.9 % Sodium Chloride Injection.
  - The intravenous administration port of the 0.9% Sodium Chloride Injection container must be penetrated only one time.
  - Strap the saline tag provided with the CardioGen-82 Infusion System on the additive-free 0.9% Sodium Chloride Injection container and install on the CardioGen-82 Infusion System.
  - Once the container port closure is penetrated, it should remain installed on the CardioGen-82 Infusion System for its entire period of use. A maximum of 12 hours from the initial port closure penetration is permitted, after which the bag must be replaced for the next patient.
- Allow at least 10 minutes between elutions for regeneration of Rb 82.
- If the CardioGen-82 Infusion System Model 510 is used:
  - Discard the first 50 mL eluate each day the generator is eluted and employ proper safety precautions since the eluate contains radioactivity.
  - Maintain an on-going record of all eluate volumes (washing, testing, dosing volumes), including a summary of the cumulative volume of eluate from the generator.
  - Perform eluate testing according to the Eluate Testing Protocol for Infusion System Model 510 [see Dosage and Administration (2.6)].
- If the CardioGen-82 Infusion System Model 1700 is used:
  - The system software automatically discards the first 50 mL of eluate each day the generator is eluted and records and saves all eluate volumes (all flushing, quality control (QC) testing, and patient infusions), representing the cumulative volume of eluate each day the generator is eluted.
  - Perform eluate testing according to the Eluate Testing Protocol for Infusions System Model 1700 [see Dosage and Administration (2.7)].
- Stop using the generator when the expiration limits are reached [see Dosage and Administration (2.8)].
- The maximum available activity of Rb 82 (dose delivery limit) will decrease as the generator ages. See Table 3 for the estimated maximum available Rb 82 activity as a function of generator age [see Dosage and Administration (2.9)].

2.6 Eluate Testing Protocol for Infusion System Model 510

Use only additive-free 0.9% Sodium Chloride Injection for all elutions [see Warnings and Precautions (5.1)].

Observe aseptic technique throughout.

Follow all instructions in the CardioGen-82 Infusion System Model 510 Operator’s Manual for performing all eluate testing as described.

Before administering Rubidium Chloride Rb 82 Injection to the first patient each day, perform the following testing:

Strontium Alert Limits and Mandatory Eluate Testing:

- Use an ionization chamber-type dose calibrator for eluate testing.
- Daily, before administering Rubidium Chloride Rb 82 Injection to any patient, perform an eluate testing to determine Rb 82, Sr 82, and Sr 85 levels
- Perform additional daily eluate tests after detecting any of the following Alert Limits:
  - 14 L total elution volume has passed through the generator column, or
  - Sr 82 level reaches 0.002 microCi per mCi Rb 82, or
  - Sr 85 level reaches 0.02 microCi per mCi Rb 82.
- Perform the additional daily eluate tests at time points determined by the day’s elution volume; tests are performed every 750 mL.
  - For example, if an Alert Limit were reached and the clinical site eluted less than 750 mL from the generator during the day, then no additional eluate tests would have been performed that day.
  - If the same clinical site the next day eluted 1,500 mL from the generator, then the site would have performed three tests that day: 1) the required daily test that precedes any patient dosing, 2) a test at the 750 mL elution point, and 3) a test at the 1,500 mL elution points.
  - If a generator’s Alert Limit is reached, the clinical site performs the additional daily tests (at intervals of 750 mL) each subsequent day the generator is used. The additional tests are necessary to promptly detect excessive Sr 82 and/or Sr 85 in eluates.

Rubidium Eluate Level Testing:

1. Set a dose calibrator for Rb 82 as recommended by the manufacturer or use the Co-60 setting and divide the reading obtained by 0.548. Obtain the reading from the instrument in millicuries.
2. Elute the generator with 50 mL of 0.9% Sodium Chloride Injection and discard the eluate (first elution).
3. Allow at least 10 minutes for the regeneration of Rb 82, then elute the generator with 50 mL of 0.9% Sodium Chloride Injection at a rate of 50 mL/min and collect the eluate in a stoppered glass vial (plastic containers are not suitable). Note the exact time of end of elution (E.O.E.).
4. Using the dose calibrator, determine the activity of Rb 82 and note the time of the reading. Correct the reading for decay to the E.O.E. using the appropriate decay factor for Rb 82 (see Table 1). Note: If the reading is taken 2 ½ minutes after end of elution, multiply the dose calibrator reading by 4 to correct for decay.
  Strontium Eluate Level Testing:
5. Using the sample obtained for the Rb 82 activity determination, allow the sample to stand for at least one hour to allow for the complete decay of Rb 82.
6. Measure the activity of the sample in a dose calibrator at the setting recommended by the manufacturer for Rb 82 and/or Sr 82. As an alternative, use the Co-60 setting and the reading obtained divided by 0.548. Set the instrument to read in microcuries and record in the display.
7. Calculate the ratio (R) of Sr 85/Sr 82 on the day (post-calibration) of the measurement using the ratio of Sr 85/Sr 82 on the day of calibration provided on the generator label and the Sr 85/Sr 82 Ratio Factor from Table 2. Determine R using the following equation:
  [Sr 85]
  R= ———— on calibration date X Ratio Factor on the day (post-calibration) of measurement
  [Sr 82]
8. Use a correction factor (F) of 0.478 to compensate for the contribution of Sr 85 to the reading.
9. Calculate the amount of Sr 82 in the sample using the following equation:
  dose calibration reading (microCi)
  Sr 82 (microCi) = —————————————
  [1 + (R) (F)]
  Example: dose calibrator reading (microCi) = 0.8; Sr85/Sr82 ratio (R) = 1.48; correction factor (F) = 0.478.
  0.8
  Sr 82 (microCi) = ———————— = 0.47
  [1 + (1.48) (0.478)]
10. Determine if Sr 82 in the eluate exceeds an Alert or Expiration Limit by dividing the microCi of Sr 82 by the mCi of Rb 82 at End of Elution (see below for further instructions based on the Sr 82 level)
  Example: 0.47 microCi or Sr 82; 50 mCi of Rb 82 E.O.E.
  0.47 microCi Sr 82
  ———————— = 0.0094 microCi/mCi Rb 82 (is above Alert Limit of 0.002; additional daily eluate
  50 mCi Rb 82 testing must be performed)
11. Determine if Sr 85 in the eluate exceeds an Alert or Expiration Limit by multiplying the result obtained in step 10 by (R) as calculated in step 7 (above).
  Example: 0.0094 x 1.48 = 0.014 microCi Sr 85/mCi Rb 82 (test result is below Alert and Expiration Limits)

Use Table 1 to calculate the decay factor for Rb 82; step 4 (above).

Table 1. Physical Decay Chart: Rb 82 half-life 75 seconds
Seconds | Fraction Remaining | Seconds | Fraction Remaining
0* | 1 | 165 | 0.218
15 | 0.871 | 180 | 0.19
30 | 0.758 | 195 | 0.165
45 | 0.66 | 210 | 0.144
60 | 0.574 | 225 | 0.125
75 | 0.5 | 240 | 0.109
90 | 0.435 | 255 | 0.095
105 | 0.379 | 270 | 0.083
120 | 0.33 | 285 | 0.072
135 | 0.287 | 300 | 0.063
150 | 0.25
*Elution time

Use Table 2 to calculate the ratio (R) of Sr 85/Sr 82; step 7 (above).

Table 2. Sr 85/Sr 82 Ratio Chart (Sr 85 T½ = 65 days, Sr 82 T½ = 25 days)
Days | Ratio; Factor | Days | Ratio; Factor | Days | Ratio; Factor
0* | 1 | 15 | 1.29 | 30 | 1.67
1 | 1.02 | 16 | 1.31 | 31 | 1.7
2 | 1.03 | 17 | 1.34 | 32 | 1.73
3 | 1.05 | 18 | 1.36 | 33 | 1.76
4 | 1.07 | 19 | 1.38 | 34 | 1.79
5 | 1.09 | 20 | 1.41 | 35 | 1.82
6 | 1.11 | 21 | 1.43 | 36 | 1.85
7 | 1.13 | 22 | 1.46 | 37 | 1.88
8 | 1.15 | 23 | 1.48 | 38 | 1.91
9 | 1.17 | 24 | 1.51 | 39 | 1.95
10 | 1.19 | 25 | 1.53 | 40 | 1.98
11 | 1.21 | 26 | 1.56 | 41 | 2.01
12 | 1.23 | 27 | 1.58 | 42 | 2.05
13 | 1.25 | 28 | 1.61
14 | 1.27 | 29 | 1.64
*Day of calibration

2.7 Eluate Testing Protocol for Infusion System Model 1700

Use only additive-free 0.9% Sodium Chloride Injection for all elutions [see Warnings and Precautions (5.1)].

Observe aseptic technique throughout.

Follow all instructions in the CardioGen-82 Infusion System Model 1700 Operator’s Manual for performing all eluate testing as described.

Perform Mandatory Eluate Testing to determine Rb 82, Sr 82, and Sr 85 levels:

1. Daily – Before administering Rubidium Chloride Rb 82 Injection to the first patient each day.
2. Repeat as indicated after an Alert Limit has been detected.
  Alert Limits:
  - 14 L total elution volume has passed through the generator column, or
  - Sr 82 level reaches 0.002 microCi per mCi Rb 82, or
  - Sr 85 level reaches 0.02 microCi per mCi Rb 82.
3. The CardioGen-82 Infusion System Model 1700 will automatically indicate when alert limits have been reached, and will require that additional tests be performed, to facilitate the prompt detection of excessive levels of Sr 82 and/or Sr 85 should they occur.
4. These additional daily eluate tests will be performed at intervals determined by the day’s elution volume and will be enforced by the System software. Specifically, the infusion system will require the user to perform additional eluate testing after each 750 mL of elution volume when any Alert Limit parameter has been reached.

Infusion System Calibration: Before administering Rubidium Chloride Rb 82 Injection to the first patient:

After installation of a new generator and / or installation of a new CardioGen-82 Accessory Package, Item # 001710, perform the Rubidium Chloride Rb 82 Injection Dose Calibration (performed using an external dose calibrator).

1. Set a dose calibrator for Rb 82 as recommended by the manufacturer. Obtain the reading from the instrument in millicuries.
2. Following the prompts in the Graphical User Interface (GUI) for the CardioGen-82 Infusion System Model 1700, elute the generator with additive-free 0.9% Sodium Chloride Injection at a rate of 50 mL/min and collect the eluate in the stoppered vial specifically provided for use with the CardioGen-82 Infusion System Model 1700 (alternative vials, glass or plastic are not suitable). Note the exact time of end of elution (EOE).
3. Using the external dose calibrator, assay the eluate at exactly 2:30, 3:45, or 5:00 minutes after EOE.
4. Following the prompts in the GUI for the CardioGen-82 Infusion System Model 1700, enter the Rb 82 reading from the dose calibrator and the time since EOE.
5. The infusion system software will automatically calculate the Calibration Ratio.
  - If the ratio is within +/- 2% (0.98 to 1.02), the infusion system will allow acceptance of the calibration factor that was used for the elution.
  - If the ratio is not within +/- 2% (0.98 to 1.02), the system requires another calibration elution (steps 1 through 4).
6. Repeat steps 1 through 4 for a flow rate of 20 mL/min.

Perform additional system calibration every 14 days.

Daily Quality Control: Eluate (Strontium Level) Testing and Dose Constancy

Each day, before administering Rubidium Chloride Rb 82 Injection, perform the following test, including Mandatory Eluate Testing:

Daily Quality Control (performed on-board the CardioGen-82 Infusion System Model 1700, using the gamma (Sr) detector):

1. Place the stoppered vial, which is specifically provided for use with the CardioGen-82 Infusion System, Model 1700 (alternative vials, glass or plastic are not suitable) in the Sr detector well on the CardioGen-82 Infusion System Model 1700 and, following the prompts in the GUI for the infusion system, initiate the Daily Quality Control workflow.
2. The infusion system will automatically perform the Sr Detector Background Reading.
3. The infusion system will automatically perform the Generator Column Wash.
4. Strontium Level Test and Dose Constancy:
  1. The infusion system will elute the generator with 50 mL of additive-free 0.9% Sodium Chloride Injection at a rate of 50 mL/min into the stoppered vial (which is specifically provided for use with the CardioGen-82 Infusion System Model 1700).
  2. The Sr detector measures the Rb 82 and strontium in the 50 mL elution.
  3. The infusion system software will automatically calculate the Sr 82 and Sr 85 levels on the day (post calibration) of the measurement using the ratio of Sr 85/Sr 82 on the day of calibration provided on the generator label, and using the full exponential decay calculation for each, accounting for the generator’s age.
  4. Using the Rb 82 and strontium measurements, the infusion system software will automatically calculate microCi Sr 82/mCi Rb 82 and microCi Sr 85/mCi Rb 82. The GUI will automatically indicate if the results exceed Alert or Expiration Limits.
  5. The infusion system software will automatically calculate Dose Constancy.
5. Constancy Check of the Sr detector: The infusion system GUI will prompt the user to perform the constancy check of the Sr detector.
  1. Place the external constancy source in the detector well of the infusion system.
  2. The infusion system software will automatically calculate the constancy of the Sr detector versus the external constancy source when instructed.

2.8 Expiration Limits of CardioGen-82

If using the Infusion System Model 510, stop use of CardioGen-82 once any one of the following Expiration Limits is reached:

- A total elution volume of 17 L has passed through the generator column
- 42 days post calibration date
- An eluate Sr 82 level of 0.01 microCi/mCi Rb 82
- An eluate Sr 85 level of 0.1 microCi/mCi Rb 82

If using the Infusion System Model 1700, the software will automatically indicate, and will stop use of CardioGen-82, once any one of the above Expiration Limits is reached.

2.9 Dose Delivery Limit of CardioGen-82

The maximum available Rb 82 activity per elution (dose delivery limit) will decrease as the generator ages. Table 3 provides an estimate of the maximum available activity of Rb 82 as a function of generator age.

Table 3. Maximum Available Rb 82 Activity Based on Generator Age^1
Generator Age (days)^2 | Maximum Rb 82 Activity per Elution
0-17 | 60 mCi (2,220 MBq)
24 | 50 mCi (1,850 MBq)
32 | 40 mCi (1,480 MBq)
42 | 30 mCi (1,110 MBq)
^1Estimate is based on a 100 mCi (3,700 MBq) Sr 82 generator at calibration.
^2Generator age at which delivery limit is reached varies with generator activity at release. For example, a 90 mCi (3,330 MBq) generator and a 150 mCi (5,550 MBq) generator will reach a delivery limit <60 mCi at ≥ 14 days and ≥ 33 days, respectively.

2.10 Radiation Dosimetry

The estimated absorbed radiation doses for Rb 82, Sr 82, and Sr 85 from an intravenous injection of Rubidium Chloride Rb 82 Injection are shown in Table 4.

Table 4. Estimated Absorbed Radiation Dose Coefficient in Adults
Organa,b | Rb 82 (Average for Rest and Stress) mrem/mCi (microSv/3.7MBq)c | Sr 82 mrem/microCi (microSv/3.7kBq)c | Sr 85 mrem/microCi (microSv/3.7kBq)c
Adrenals | 7.56 | 10.6 | 5.03
Bone – Osteogenic cells Bone Surface | 1.86 ---- | --- 107 | --- 9.81
Brain | 0.6 | 8.29 | 2.96
Breast | 0.82 | 7.03 | 1.72
Gall Bladder Wall | 3.17 | 8.47 | 2.82
Heart Wall | 16.5 | 8.18 | 2.67
Kidneys | 20.04 | 9.18 | 2.5
Liver | 4.2 | 8.10 | 2.5
Lower Large Intestine Wall | 2.84 | 51.8 | 5.14
Lungsd | 10.7 | 8.25 | 2.84
Muscles | 1.29 | 8.14 | 2.66
Ovaries | 1.41 | 10.2 | 4.29
Pancreas | 8.85 | 9.1 | 3.46
Red Marrow | 1.19 | 91 | 9.84
Skin | 1.14 | 7.03 | 1.75
Small Intestine | 4.76 | 9.62 | 4.03
Spleen | 6.61 | 8.1 | 2.54
Stomach | 8.14 | 7.84 | 2.26
Testes | 0.82 | 7.25 | 1.7
Thymus | 1.49 | 7.84 | 2.33
Thyroid | 6.11 | 8.07 | 2.57
Upper Large Intestine | 5.94 | 23.7 | 3.62
Urinary Bladder Wall | 1.61 | 21.9 | 2.9
Uterus | 3.72 | 9.14 | 3.32
Total Body | 1.77 | Not calculated | Not calculated
Effective Dosee | 4.74f | 23.4 | 4.03
a Rb 82 doses are averages of rest and stress dosimetry data. To calculate organ doses (mrem) from Rb 82, multiply the dose coefficient for each organ by the administered activity in mCi.
b Sr 82 and Sr 85 doses are calculated using software package DCAL and ICRP dose coefficients. To calculate organ doses (mrem) attributable to Sr 82, and Sr 85, multiply the dose coefficients by the calculated amounts of strontium in microCi.
c To convert to SI units, insert the dose coefficient into the formula in parentheses, e.g. for adrenals 7.56 mrem/mCi = 7.56 microSv/37 MBq = 2.04 x 10^-13 Sv/Bq.
d Calculated from ICRP 66
e Calculated from ICRP 60
f Stress phase only

3 DOSAGE FORMS AND STRENGTHS

Rubidium Rb 82 generator used to produce Rubidium Chloride Rb 82 Injection: strontium-82 (Sr 82), with an activity of 3,330 MBq to 5,550 MBq (90 mCi to 150 mCi) at calibration time, adsorbed on a hydrous stannic oxide column.

4 CONTRAINDICATIONS

None.

5 WARNINGS AND PRECAUTIONS

5.1 High Level Radiation Exposure with Use of Incorrect Eluent

Additives present in solutions (particularly calcium ions) used by mistake to elute CardioGen-82 expose patients to high levels of radiation by causing the release of large amounts of Sr 82 and Sr 85 into the eluate regardless of the generator’s age or prior use. When solutions containing calcium ions are used, high levels of radioactivity are present in any subsequent eluate even with the use of additive-free 0.9% Sodium Chloride Injection.

Use only additive-free 0.9% Sodium Chloride Injection to elute CardioGen-82. If an incorrect eluent is used, immediately stop the patient infusion, evaluate the patient’s radiation absorbed dose, and monitor for the effects of radiation to critical organs such as bone marrow. Permanently discontinue use of the affected CardioGen-82 generator [see Dosage and Administration (2.5)].

5.2 Excess Radiation Exposure with Failure to Follow the Eluate Testing Protocol

Excess radiation exposure occurs when the Sr 82 and Sr 85 levels in the Rubidium Chloride Rb 82 Injection exceed the specified generator eluate limits.

Strictly adhere to the eluate testing protocol to minimize radiation exposure to the patient. Stop using the CardioGen-82 generator when the expiration limits are reached [see Dosage and Administration (2.6, 2.7, 2.8)].

5.3 Risks Associated with Pharmacologic Stress

Pharmacologic induction of cardiovascular stress may be associated with serious adverse reactions such as myocardial infarction, arrhythmia, hypotension, bronchoconstriction, and cerebrovascular events. Perform pharmacologic stress testing in accordance with the pharmacologic stress agent’s prescribing information and only in the setting where cardiac resuscitation equipment and trained staff are readily available.

5.4 Cumulative Radiation Exposure: Long-Term Risk of Cancer

Rubidium chloride Rb 82 contributes to a patient’s overall long-term cumulative radiation exposure. Long-term cumulative radiation exposure is associated with an increased risk of cancer. Use the lowest dose of Rubidium Chloride Rb 82 Injection necessary for imaging and ensure safe handling to protect the patient and health care providers. Encourage patients to void as soon as a study is completed and as often as possible thereafter for a least one hour [see Dosage and Administration (2.1, 2.2)].

6 ADVERSE REACTIONS

The following clinically significant adverse reactions are described elsewhere in the labeling:

- High Level Radiation Exposure with Use of Incorrect Eluent [see Warnings and Precautions (5.1)]
- Excess Radiation Exposure with Failure to Follow Eluate Testing Protocol [see Warnings and Precautions (5.2)]

The following serious adverse reactions have been identified during post-approval use of CardioGen-82. Because these reactions are reported voluntarily from a population of uncertain size, it is not always possible to reliably estimate their frequency or establish a causal relationship to drug exposure.

Radiation Exposure

High level radiation exposure to the bone marrow from using an incorrect eluent.
Excess radiation exposure due to insufficient eluate testing.

8 USE IN SPECIFIC POPULATIONS

8.1 Pregnancy

Risk Summary

There are no data available on the use of rubidium chloride Rb 82 in pregnant women. Animal reproductive studies have not been conducted with rubidium chloride Rb 82. However, all radiopharmaceuticals, including Rubidium Chloride Rb 82 Injection generated by CardioGen-82, have the potential to cause fetal harm depending on the fetal stage of development and the magnitude of the radiation dose. If considering Rubidium Chloride Rb 82 Injection administration to a pregnant woman, inform the patient about the potential for adverse pregnancy outcomes based on the radiation dose from rubidium-82 (Rb 82) and the gestational timing of exposure.

The estimated background risk of major birth defects and miscarriage for the indicated population is unknown. In the U.S. general population, the estimated background risk of major birth defects and miscarriage in clinically recognized pregnancies is 2% to 4% and 15% to20%, respectively.

8.2 Lactation

Risk Summary

There is no information regarding the presence of rubidium chloride Rb 82 in human milk, the effects on the breastfed infant or the effects on milk production. Due to the short half-life of Rb 82 (75 seconds), exposure of a breastfed infant through breast milk can be minimized by temporary discontinuation of breastfeeding (see Clinical Considerations). The developmental and health benefits of breastfeeding should be considered along with the mother’s clinical need for Rubidium Chloride Rb 82 Injection, any potential adverse effects on the breastfed child from Rb 82 or from the underlying maternal condition.

Clinical Considerations

Exposure to Rb 82 through breast milk can be minimized if breastfeeding is discontinued when Rubidium Chloride Rb 82 Injection is administered. Do not resume breastfeeding until at least one hour after administration of Rubidium Chloride Rb 82 Injection.

8.4 Pediatric Use

The safety and effectiveness of CardioGen-82, used to produce Rubidium Chloride Rb 82 Injection, in pediatric patients have not been established.

8.5 Geriatric Use

In elderly patients with a clinically important decrease in cardiac function, lengthen the delay between infusion and image acquisition [see Dosage and Administration (2.3)]. Observe for the possibility of fluid overload.

11 DESCRIPTION

11.1 Generator Characteristics

CardioGen-82 (rubidium Rb 82 generator) contains accelerator-produced Sr 82 adsorbed on stannic oxide in a lead-shielded column and provides a means to produce sterile nonpyrogenic Rubidium Chloride Rb 82 Injection, a radioactive diagnostic agent, for intravenous use. The chemical form of Rb 82 is ^82RbCl.

The amount (mCi) of Rb 82 obtained in each elution will depend on the potency of the generator. When eluted at a rate of 50 mL/minute, each generator eluate at the end of elution should not contain more than 0.02 microCi of Sr 82 and not more than 0.2 microCi of Sr 85 per mCi of Rubidium Chloride Rb 82 Injection, and not more than 1 mcg of tin per mL of eluate.

11.2 Nuclear Physical Characteristics

Rb 82 decays by positron emission and associated gamma emission with a physical half-life of 75 seconds. Table 5 shows the annihilation photons released following positron emission which are useful for detection and imaging studies.

The decay modes of Rb 82 are: 95.5% by positron emission, resulting in the production of annihilation radiation, i.e., two 511 keV gamma rays; and 4.5% by electron capture, resulting in the emission of “prompt” gamma rays of predominantly 776.5 keV. Both decay modes lead directly to the formation of stable krypton 82 (Kr 82).

Table 5. Principal Radiation Emission Data for Rb 82
Radiation | Mean Percent Per Disintegration | Mean Energy (keV)
Annihilation photons (2) | 191.01 | 511 (each)
Gamma rays | 13-15 | 776.5

The specific gamma ray constant for Rb 82 is 6.1 R/hour-mCi at 1 cm. The first half-value layer is 0.7 cm of lead (Pb). Table 6 shows a range of values for the relative attenuation of the radiation emitted by this radionuclide that results from interposition of various thicknesses of lead. For example, the use of a 7.0 cm thickness of Pb will attenuate the radiation emitted by a factor of about 1,000.

Table 6. Radiation Attenuation by Lead Shielding
Shield Thickness (Pb) cm | Attenuation Factor
0.7 | 0.5
2.3 | 10^-1
4.7 | 10^-2
7.0 | 10^-3
9.3 | 10^-4

Sr 82 (half-life of 25 days (600 hrs.) decays to Rb 82. To correct for physical decay of Sr 82, Table 7 shows the fractions that remain at selected intervals after the time of calibration.

Table 7. Physical Decay Chart: Sr 82 half-life 25 days
Days | FractionRemaining | Days | FractionRemaining | Days | FractionRemaining
0* | 1 | 15 | 0.660 | 30 | 0.435
1 | 0.973 | 16 | 0.642 | 31 | 0.423
2 | 0.946 | 17 | 0.624 | 32 | 0.412
3 | 0.920 | 18 | 0.607 | 33 | 0.401
4 | 0.895 | 19 | 0.591 | 34 | 0.390
5 | 0.871 | 20 | 0.574 | 35 | 0.379
6 | 0.847 | 21 | 0.559 | 36 | 0.369
7 | 0.824 | 22 | 0.543 | 37 | 0.359
8 | 0.801 | 23 | 0.529 | 38 | 0.349
9 | 0.779 | 24 | 0.514 | 39 | 0.339
10 | 0.758 | 25 | 0.500 | 40 | 0.330
11 | 0.737 | 26 | 0.486 | 41 | 0.321
12 | 0.717 | 27 | 0.473 | 42 | 0.312
13 | 0.697 | 28 | 0.460
14 | 0.678 | 29 | 0.448
*Calibration time

To correct for physical decay of Rb 82, Table 1 shows the fraction of Rb 82 remaining in all 15 second intervals up to 300 seconds after time of calibration [see Dosage and Administration (2.6, 2.7)].

12 CLINICAL PHARMACOLOGY

12.1 Mechanism of Action

Rb 82 is analogous to potassium ion (K^+) in its biochemical behavior and is extracted by the myocardium in proportion to the blood flow. Rb^+ participates in the sodium-potassium (Na^+/K^+) ion exchange pumps that are present in cell membranes. The intracellular uptake of Rb 82 requires maintenance of ionic gradient across cell membranes. Rb 82 radioactivity is increased in viable myocardium reflecting intracellular retention, while the tracer is cleared from necrotic or infarcted tissue.

12.2 Pharmacodynamics

In human studies, myocardial activity was noted within the first minute after peripheral intravenous injection of rubidium chloride Rb 82. When areas of infarction or ischemia are present in the myocardium, they are visualized within 2 minutes to 7 minutes after injection as photon-deficient, or “cold”, areas on the myocardial scan. In patients with reduced cardiac function, transit of the injected dose from the peripheral infusion site to the myocardium may be delayed [see Dosage and Administration (2.3)].

Blood flow brings Rb 82 to all areas of the body during the first pass of circulation. Accordingly, visible uptake is also observed in other highly vascularized organs, such as the kidneys, liver, spleen, and lungs.

12.3 Pharmacokinetics

With a physical half-life of 75 seconds, Rb 82 is converted by radioactive decay into stable Kr 82 gas, which is passively expired by the lungs.

13 NONCLINICAL TOXICOLOGY

13.1 Carcinogenesis, Mutagenesis, Impairment of Fertility

No long-term studies have been performed to evaluate carcinogenic potential, mutagenicity potential, or to determine whether rubidium chloride Rb 82 may affect fertility in males or females.

14 CLINICAL STUDIES

In a descriptive, prospective, blinded image interpretation study of adult patients with known or suspected coronary artery disease, myocardial perfusion deficits in stress and rest PET images obtained with ammonia N 13 (n = 111) or rubidium chloride Rb 82 (n = 82) were compared to changes in stenosis flow reserve (SFR) as determined by coronary angiography. PET perfusion defects at rest and stress for seven cardiac regions (anterior, apical, anteroseptal, posterolateral, anterolateral, posterolateral, and inferior walls) were graded on a scale of 0 (normal) to 5 (severe). Values for stenosis flow reserve, defined as flow at maximum coronary vasodilatation relative to rest flow, ranged from 0 (total occlusion) to 5 (normal). With increasing impairment of flow reserve, the subjective PET defect severity increased. A PET defect score of 2 or higher was positively correlated with flow reserve impairment (SFR<3).

A systematic review of published literature was conducted using pre-defined inclusion/exclusion criteria which resulted in identification of 10 studies evaluating the use of Rb 82 PET myocardial perfusion imaging (MPI) for the identification of coronary artery disease as defined by catheter-based angiography. In these studies, the patient was the unit of analysis and 50% stenosis was the threshold for clinically significant coronary artery disease (CAD). Of these 10 studies, 9 studies were included in a meta-analysis for sensitivity (excluding one study with 100% sensitivity) and 7 studies were included in a meta-analysis of specificity (excluding 3 studies with 100% specificity). A random effects model yielded overall estimates of sensitivity and specificity of 92% (95% CI: 89% to 95%) and 81% (95% CI: 76% to 86%), respectively. The use of meta-analysis in establishing performance characteristics is limited, particularly by the possibility of publication bias (positive results being more likely to be published than negative results) which is difficult to detect especially when based on a limited number of small studies.

16 HOW SUPPLIED/STORAGE AND HANDLING

How Supplied

CardioGen-82 (rubidium Rb 82 generator), used to produce Rubidium Chloride Rb 82 Injection, is supplied in a lead shield surrounded by a labeled plastic container with an activity at calibration time of 3,330 MBq to 5,550 MBq (90 mCi to 150 mCi) of Sr 82 adsorbed on a hydrous stannic oxide column (NDC 0270-0091-01).

The container label provides complete assay data for each generator.

Storage and Handling

Store the generator at 20°C to 25°C (68°F to 77°F) [See USP Controlled Room Temperature].

- Receipt, transfer, possession, storage, disposal or use of this product is subject to the radioactive material regulations and licensing requirements of the U.S. Nuclear Regulatory Commission (NRC), Agreement States or Licensing States as appropriate. Do not dispose of the generator in regular refuse systems. This generator is approved for use by persons licensed by the Illinois Emergency Management Agency pursuant to Section 330.260(a), (b) or (c) and 32 Ill. Adm. Code 335.4010 or under equivalent licenses of NRC or an Agreement State.

For questions about the disposal of the CardioGen-82 generator, contact Bracco Diagnostics Inc. at 1-800-447-6883, option 3.

17 PATIENT COUNSELING INFORMATION

Post-Study Voiding

Instruct patients to void after completion of each image acquisition session and as often as possible for one hour after completion of the PET scan [see Warnings and Precautions (5.4)].

Pregnancy

Advise a pregnant woman of the potential risk to a fetus [see Use in Specific Populations (8.1)].

Lactation

Advise lactating women that exposure to Rb 82 through breast milk can be minimized if breastfeeding is discontinued when Rubidium Chloride Rb 82 Injection is administered. Advise lactating women not to resume breastfeeding for at least one hour after administration of Rubidium Chloride Rb 82 Injection [see Use in Specific Populations (8.2)].

Manufactured for
Bracco Diagnostics Inc.
Princeton, NJ 08540

Manufactured By
GE Healthcare, Medi-Physics, Inc.
Arlington Heights, IL 60004

CardioGen-82® Rubidium 82 Generators, Infusion Systems, and Accessories contain proprietary technology covered by one or more patents listed at www.braccoimaging.com/us-en/patents.

PACKAGE LABEL

CardioGen-82
NDC: 0270–0091–01
Rubidium Rb 82 Generator